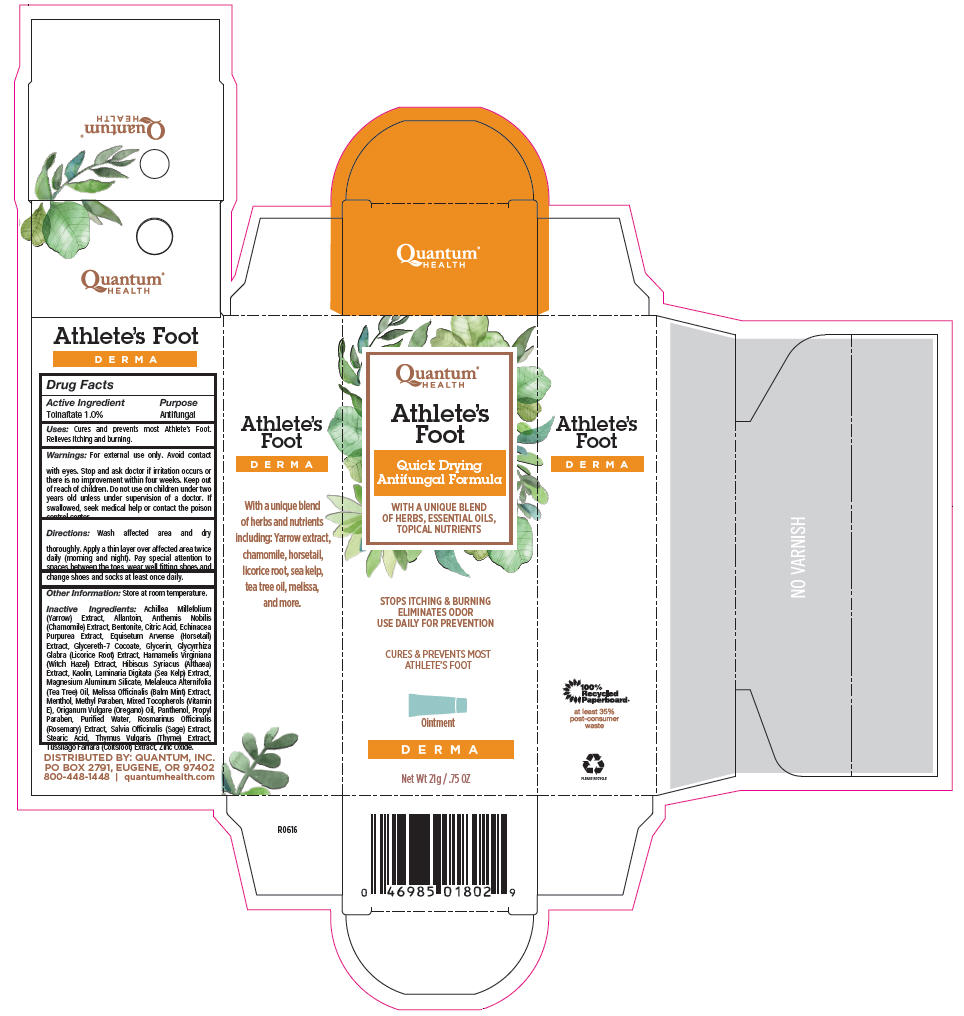 DRUG LABEL: Athletes Foot
NDC: 70084-510 | Form: CREAM
Manufacturer: Quantum, Inc.
Category: otc | Type: HUMAN OTC DRUG LABEL
Date: 20251020

ACTIVE INGREDIENTS: TOLNAFTATE 10 mg/1 g
INACTIVE INGREDIENTS: ECHINACEA PURPUREA; TEA TREE OIL; MENTHOL, UNSPECIFIED FORM; TOCOPHEROL; WATER; ALLANTOIN; CHAMOMILE; BENTONITE; CITRIC ACID MONOHYDRATE; EQUISETUM ARVENSE TOP; PEG-7 GLYCERYL COCOATE; GLYCERIN; GLYCYRRHIZA GLABRA; HIBISCUS SYRIACUS BARK; HAMAMELIS VIRGINIANA TOP; KAOLIN; LAMINARIA DIGITATA; MAGNESIUM ALUMINUM SILICATE; MELISSA OFFICINALIS; METHYLPARABEN; OREGANO LEAF OIL; PANTHENOL; PROPYLPARABEN; ROSEMARY; SAGE; STEARIC ACID; THYME; TUSSILAGO FARFARA FLOWER; ZINC OXIDE

Athlete's Foot

Drug Facts

Active Ingredient

Tolnaftate 1.0%

Purpose

Antifungal

Uses

Cures and prevents most Athlete's Foot. Relieves itching and burning.

Warnings

For external use only. Avoid contact with eyes. Stop and ask doctor if irritation occurs or there is no improvement within four weeks.

Keep out of reach of children. Do not use on children under two years old unless under supervision of a doctor. If swallowed, seek medical help or contact the poison control center.

Directions

Wash affected area and dry thoroughly. Apply a thin layer over affected area twice daily (morning and night). Pay special attention to spaces between the toes, wear well fitting shoes and change shoes and socks at least once daily.

Other Information

Store at room temperature.

Inactive Ingredients

Achillea Millefolium (Yarrow) Extract, Allantoin, Anthemis Nobilis (Chamomile) Extract, Bentonite, Citric Acid, Echinacea Purpurea Extract, Equisetum Arvense (Horsetail) Extract, Glycereth-7 Cocoate, Glycerin, Glycyrrhiza Glabra (Licorice Root) Extract, Hamamelis Virginiana (Witch Hazel) Extract, Hibiscus Syriacus (Althaea) Extract, Kaolin, Laminaria Digitata (Sea Kelp) Extract, Magnesium Aluminum Silicate, Melaleuca Alternifolia (Tea Tree) Oil, Melissa Officinalis (Balm Mint) Extract, Menthol, Methyl Paraben, Mixed Tocopherols (Vitamin E), Origanum Vulgare (Oregano) Oil, Panthenol, Propyl Paraben, Purified Water, Rosmarinus Officinalis (Rosemary) Extract, Salvia Officinalis (Sage) Extract, Stearic Acid, Thymus Vulgaris (Thyme) Extract, Tussilago Farfara (Coltsfoot) Extract, Zinc Oxide.

DISTRIBUTED BY: QUANTUM, INC.
PO BOX 2791, EUGENE, OR 97402

PRINCIPAL DISPLAY PANEL - 21 g Tube Carton

Quantum®
HEALTH

Athlete's
Foot

Quick Drying
Antifungal Formula

WITH A UNIQUE BLEND
OF HERBS, ESSENTIAL OILS,
TOPICAL NUTRIENTS

STOPS ITCHING & BURNING
ELIMINATES ODOR
USE DAILY FOR PREVENTION

CURES & PREVENTS MOST
ATHLETE'S FOOT

Ointment

D E R M A

Net Wt 21g / .75 OZ